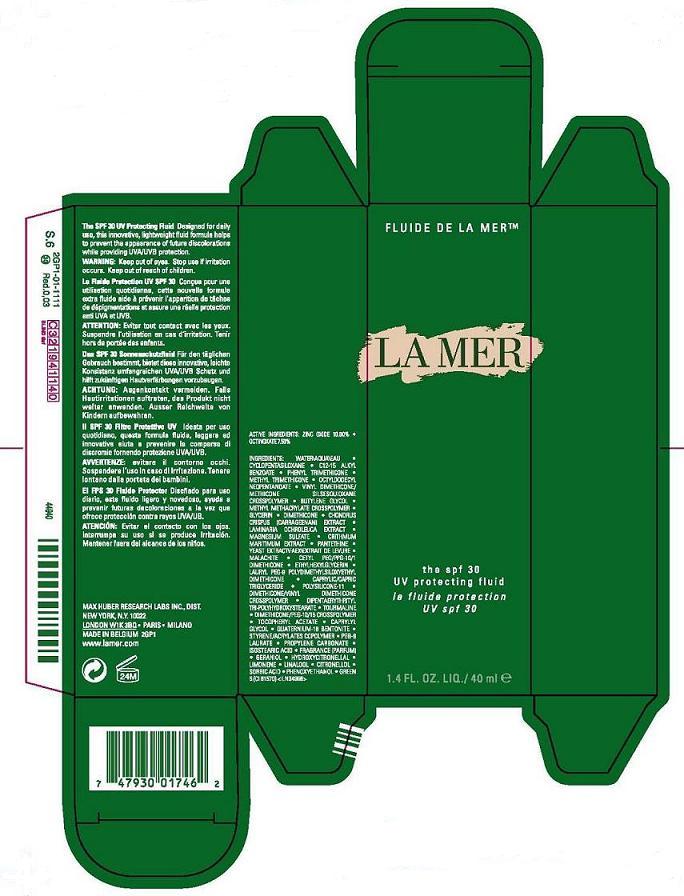 DRUG LABEL: LA MER 
NDC: 65966-009 | Form: LIQUID
Manufacturer: MAX HUBER RESEARCH LAB INC
Category: otc | Type: HUMAN OTC DRUG LABEL
Date: 20100429

ACTIVE INGREDIENTS: ZINC OXIDE 10.00 mL/100 mL; OCTINOXATE 7.5 mL/100 mL

ACTIVE INGREDIENT

ACTIVE INGREDIENTS: ZINC OXIDE 10.00% [] OCTINOXATE 7.50%

WARNINGS

WARNING: KEEP OUT OF EYES. STOP USE IF IRRITATION OCCURS. KEEP OUT OF REACH OF CHILDREN.

PACKAGE LABEL

PRINCIPALDISPLAY PANEL:

fluid de la mer
LA MER
THE SPF 30
UV PROTECTING FLUID
1.4 FL. OZ. LIQ. / 40 ML
MAX HUBER RESEARCH LAB, DIST
NEW YORK, NY 10022